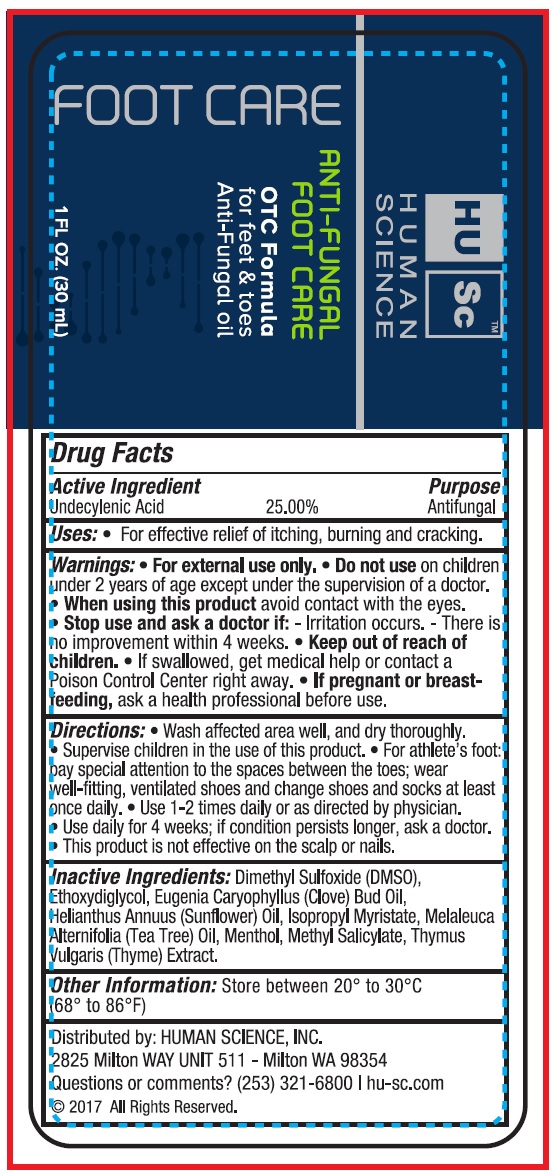 DRUG LABEL: Human Science Antifungal Foot Care
NDC: 71356-156 | Form: LIQUID
Manufacturer: HUMAN SCIENCE, LLC
Category: otc | Type: HUMAN OTC DRUG LABEL
Date: 20231105

ACTIVE INGREDIENTS: UNDECYLENIC ACID 250 mg/1 mL
INACTIVE INGREDIENTS: DIMETHYL SULFOXIDE; DIETHYLENE GLYCOL MONOETHYL ETHER; CLOVE OIL; SUNFLOWER OIL; ISOPROPYL MYRISTATE; MELALEUCA ALTERNIFOLIA LEAF; METHYL SALICYLATE; THYME

Human Science Antifungal Foot Care

Active Ingredient

Undecylenic Acid 25.00%

Purpose

Antifungal

Uses:

- For effective relief of itching, burning and cracking.

Warnings:

- For external use only.

Do not use

on children under 2 years of age except under the supervision of a doctor.

When using this product

avoid contact with the eyes.

Stop use and ask a doctor if:

-Irritation occurs.

-There is no improvement within 4 weeks.

Keep out of reach of children.

If swallowed, get medical help or contact a Poison Control Center right away.

If pregnant or breast feeding,

ask a health professional before use.

Directions:

- Wash affected area well, and dry thoroughly.
- Supervise, children in the use of this product.
- For arthlete's foot:pay special attention to the spaces between the toes; wear well-fitting, ventilated shoes and change socks at least once daily.
- Use 1-2 times daily or as directed by physician.
- Use daily for 4 weeks; if condition persists longer, ask a doctor.
- This product is not effective on the scalp or nails.

Inactive Ingredients:

Dimethyl Sulfoxid (DMSO), Ethoxydigilcol, Eugenia Caryophyllus (Clove) Bud oil, Helianthus Annuus (Sunflower) Oil, Isopropyl Myristate, Melaleuca Alternifolia (Tea Tree) Oil, Methyl Salicylate, Thymus Vulgaris (Thyme) Extract.

Other Information:

Store between 20° to 30°C (68° to 86°F)